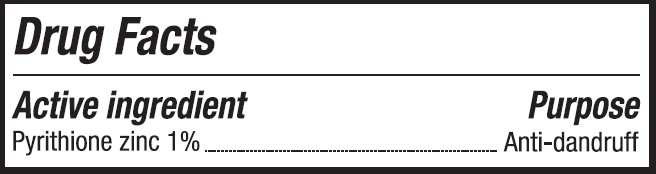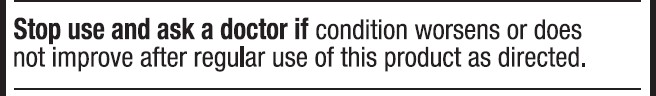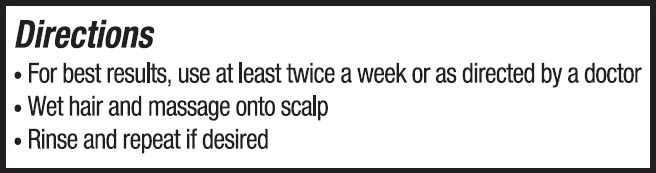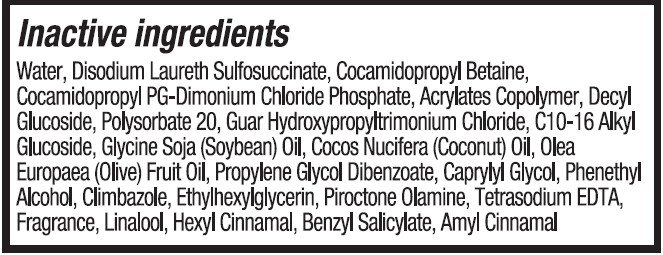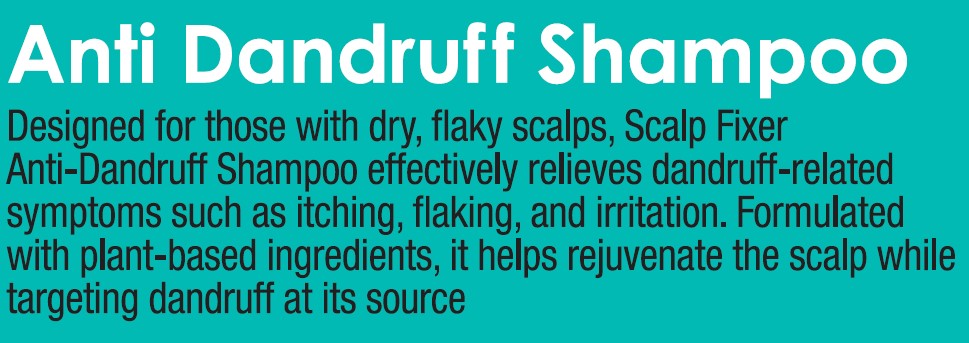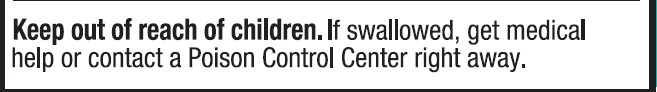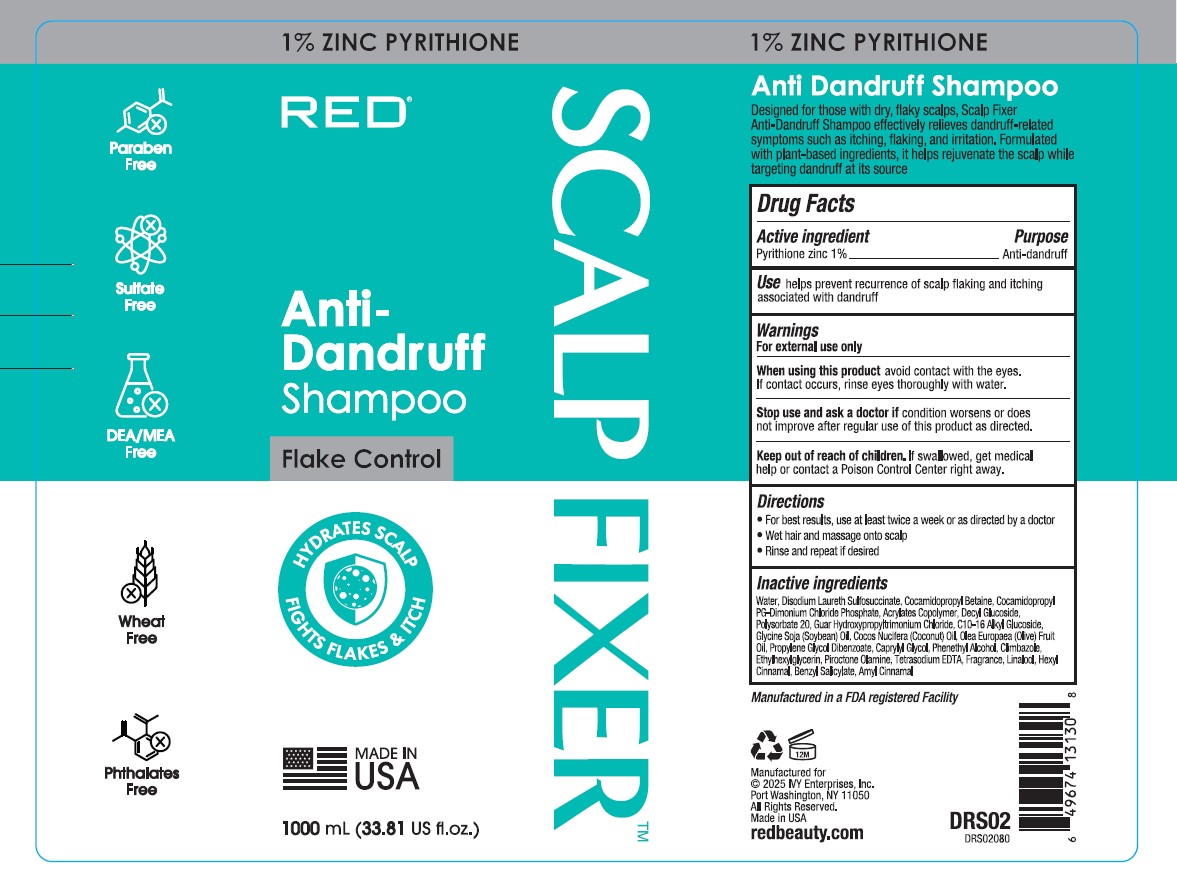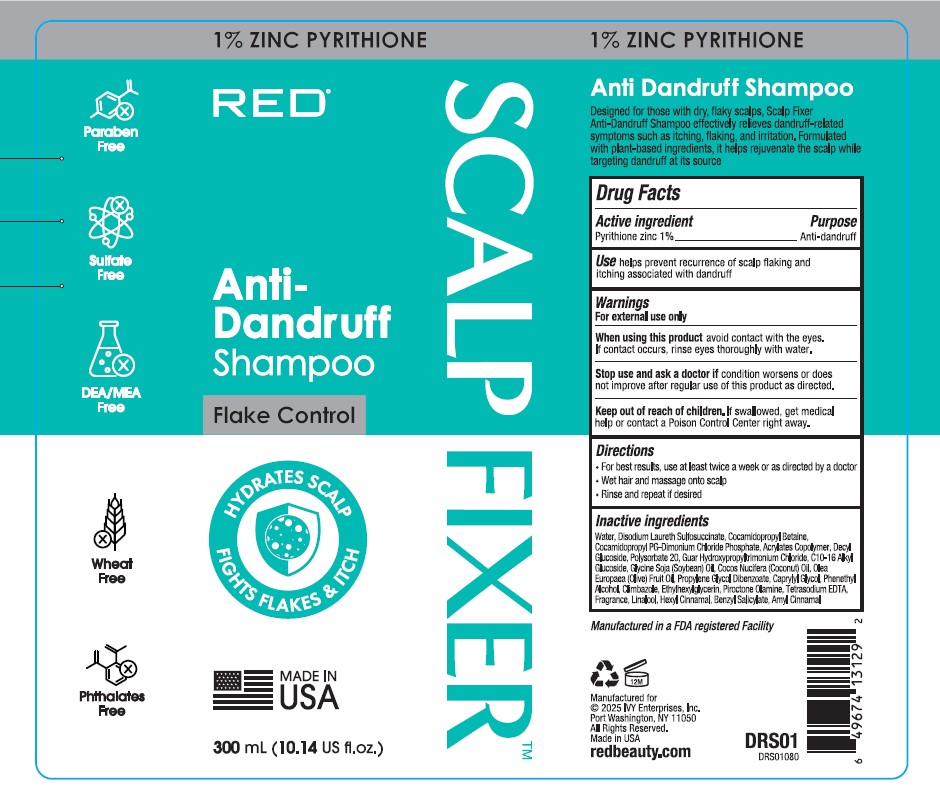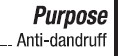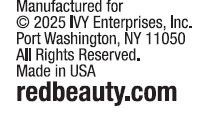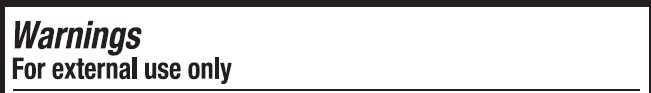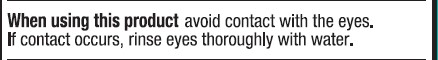 DRUG LABEL: Red Scalpfixer Anti Dandruff
NDC: 71331-120 | Form: SHAMPOO
Manufacturer: Orange Lab, Inc
Category: otc | Type: HUMAN OTC DRUG LABEL
Date: 20250701

ACTIVE INGREDIENTS: ZINC PYRITHIONE 10 mg/100 mL
INACTIVE INGREDIENTS: CLIMBAZOLE; ETHYLHEXYLGLYCERIN; PIROCTONE OLAMINE; HEXYL CINNAMAL; BENZYL SALICYLATE; AMYL CINNAMAL; OLEA EUROPAEA (OLIVE) FRUIT OIL; WATER; DISODIUM LAURETH SULFOSUCCINATE; PROPYLENE GLYCOL DIBENZOATE; CAPRYLYL GLYCOL; ACRYLATE/ISOBUTYL METHACRYLATE/N-TERT-OCTYLACRYLAMIDE COPOLYMER (75000 MW); DECYL GLUCOSIDE; POLYSORBATE 20; COCAMIDOPROPYL PG-DIMONIUM CHLORIDE PHOSPHATE; COCO-GLUCOSIDE; SOYBEAN OIL; COCONUT OIL; PHENETHYL ALCOHOL; TETRASODIUM EDTA; LINALOOL; COCAMIDOPROPYL BETAINE; GUAR HYDROXYPROPYLTRIMONIUM CHLORIDE

Red Scalpfixer Anti Dandruff Shampoo

questions

Visit readbeauty.com